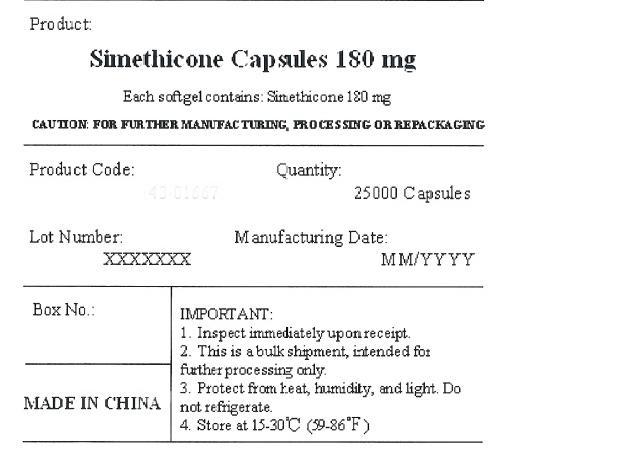 DRUG LABEL: SIMETHICONE
NDC: 84328-002 | Form: CAPSULE, LIQUID FILLED
Manufacturer: SHANDONG ROSEMED BIOOHARM LLC
Category: otc | Type: HUMAN OTC DRUG LABEL
Date: 20240826

ACTIVE INGREDIENTS: DIMETHICONE 180 mg/1 1
INACTIVE INGREDIENTS: WATER; GLYCERIN; FD&C YELLOW NO. 6

Active ingredient (in each capsule)

Simethicone 180 mg

Purpose

Anti-gas

Uses

relieves bloating, pressure or fullness commonly referred to as gas

Warnings

Stop use and ask a doctorif condition persists

Keep out of reach of children.

Other information

store at room temperature 59º - 86ºF (15º - 30ºC)

Directions

swallow one or two softgels as needed after a meal
do not exceed two softgels per day except under the advice and supervision of a physician

Inactive ingredients

FD&C yellow#6, gelatin, glycerin, purified water and white edible ink

keep out of reach of children